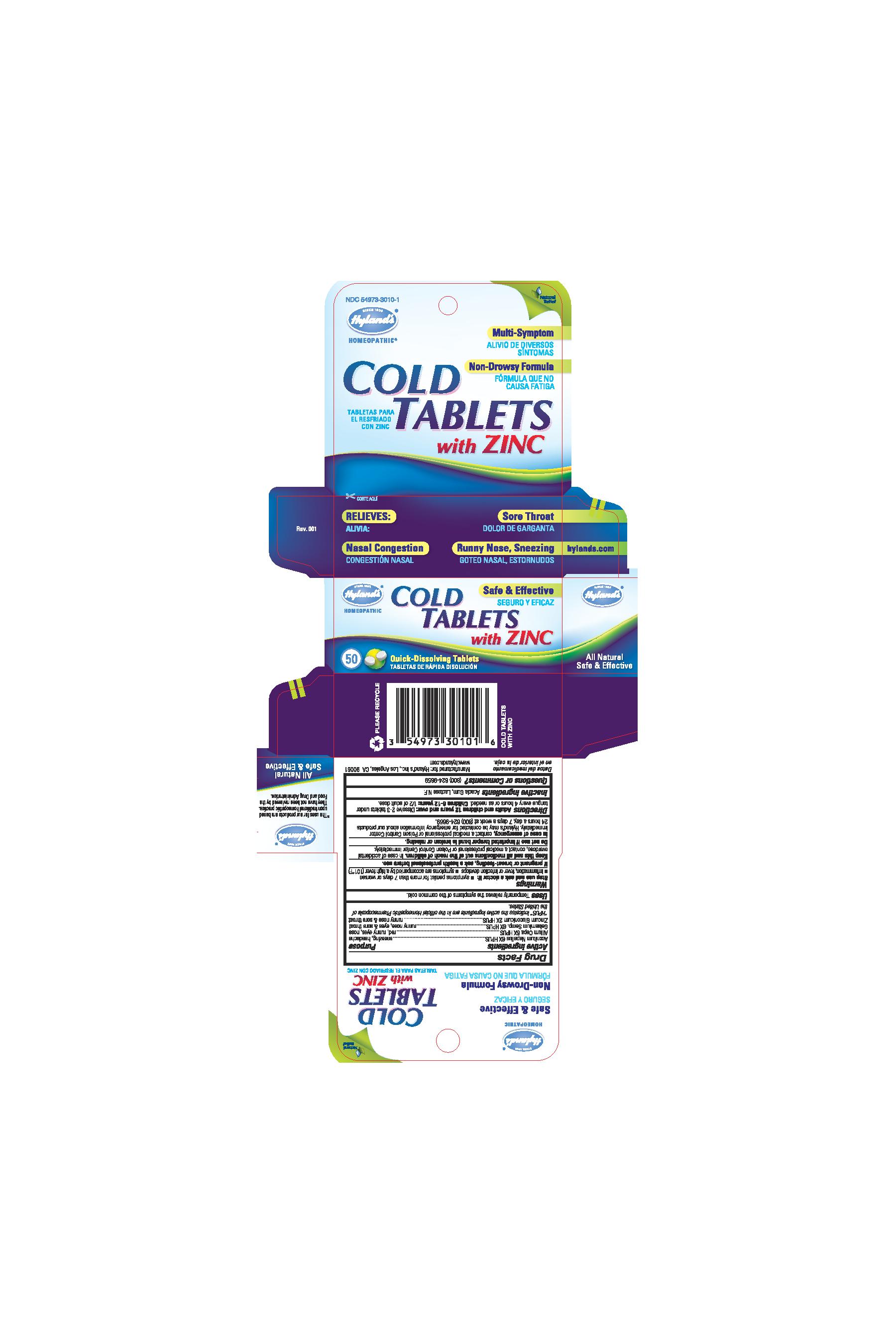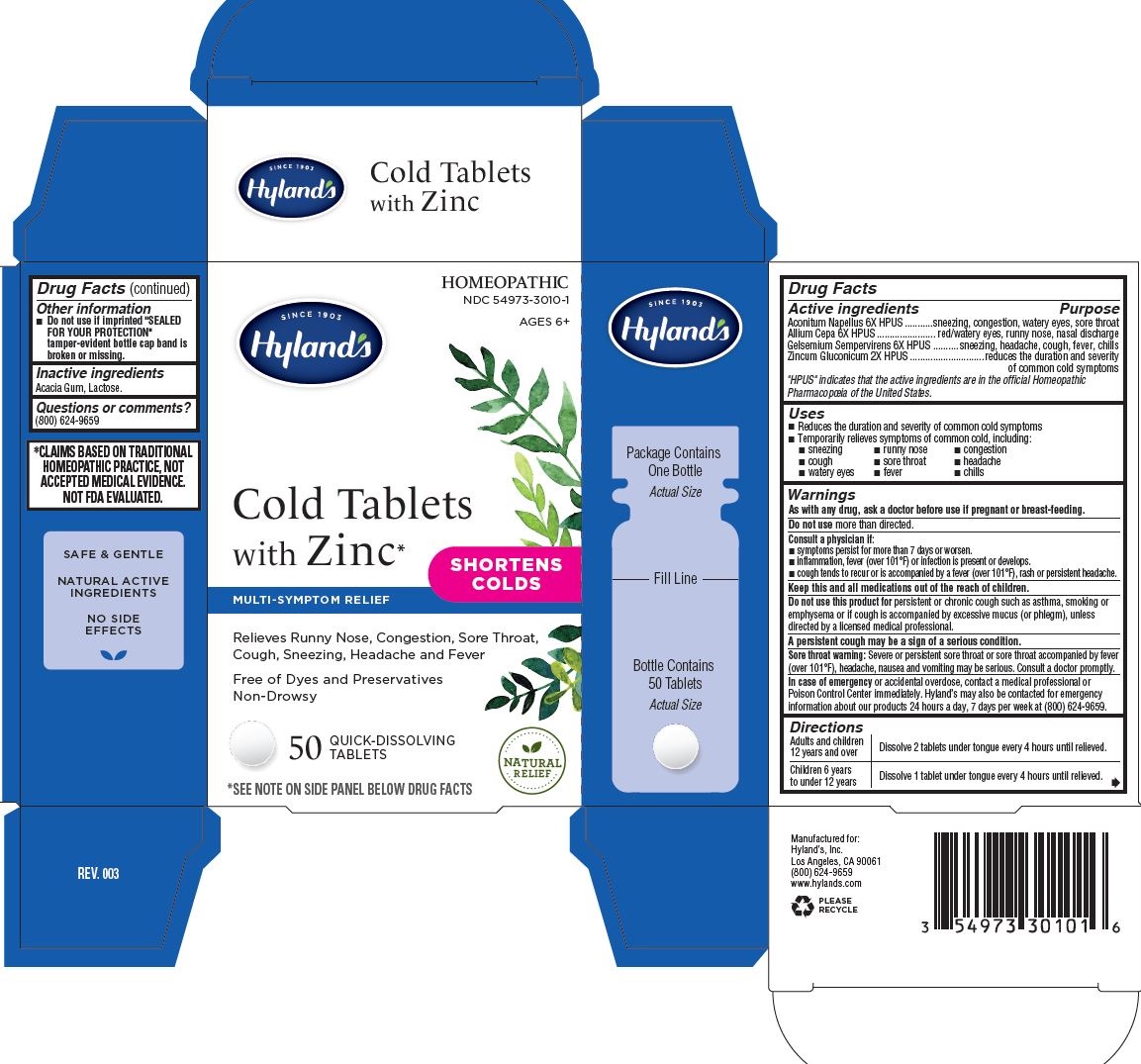 DRUG LABEL: COLD
NDC: 54973-3010 | Form: TABLET
Manufacturer: Hyland's Inc.
Category: homeopathic | Type: HUMAN OTC DRUG LABEL
Date: 20250108

ACTIVE INGREDIENTS: ACONITUM NAPELLUS 6 [hp_X]/1 g; GELSEMIUM SEMPERVIRENS ROOT 6 [hp_X]/1 g; ONION 6 [hp_X]/1 g; ZINC GLUCONATE 2 [hp_X]/1 g
INACTIVE INGREDIENTS: ACACIA; LACTOSE

Hyland's Cold Tablets with Zinc

PURPOSE

Relieves Runny Nose, Congestion, Sore Throat, Cough, Sneezing, Headache and Fever

Drug Facts

Active ingredients | Purpose
Aconitum Napellus 6X HPUS | sneezing, watery eyes, sore throat
Allium Cepa 6X HPUS | red/watery eyes, runny nose, nasal discharge
Gelsemium Sempervirens 6X HPUS | sneezing, headache, sore throat, cough
Zincum Gluconicum 2X HPUS | runny nose, sore throat

"HPUS" indicates that the active ingredients are in the official Homeopathic
Pharmacopœia of the United States.

Uses

■ Reduces the duration and severity of common cold symptoms
■ Temporarily relieves symptoms of common cold, including:
■ sneezing ■ runny nose ■ congestion
■ cough ■ sore throat ■ headache
■ watery eyes ■ fever ■ chills

Warnings

PREGNANCY OR BREAST FEEDING

As with any drug, ask a doctor before use if pregnant or breast-feeding.

Do not use more than directed.

ASK DOCTOR

Consult a physician if:

■ symptoms persist for more than 7 days or worsen.
■ inflammation, fever (over 101°F) or infection is present or develops.
■ cough tends to recur or is accompanied by a fever (over 101°F), rash or persistent headache.

KEEP OUT OF REACH OF CHILDREN

Keep this and all medications out of the reach of children.

Do not use this product for persistent or chronic cough such as asthma, smoking or emphysema or if cough is accompanied by excessive mucus, unless directed by a licensed medical professional.

A persistent cough may be a sign of a serious condition.

Sore throat warning: Severe or persistent sore throat or sore throat accompanied by fever (over 101°F), headache, nausea and vomiting may be serious. Consult a doctor promptly.

OVERDOSAGE

In case of emergency or accidental overdose, contact a medical professional or Poison Control Center immediately. Hyland’s may also be contacted for emergency information about our products 24 hours a day, 7 days per week at (800) 624-9659.

Directions

Adults and children 12 years and over | Dissolve 2 tablets under tongue every 4 hours until relieved.
Children 6 years to under 12 years | Dissolve 1 tablet under tongue every 4 hours until relieved.

Drug Facts (continued)

Other information

■ Do not use if imprinted "SEALED FOR YOUR PROTECTION" tamper-evident bottle cap band is broken or missing.

Inactive ingredients

Acacia Gum, Lactose.

Questions or comments?

(800) 624-9659

*CLAIMS BASED ON TRADITIONAL HOMEOPATHIC PRACTICE, NOT ACCEPTED MEDICAL EVIDENCE. NOT FDA EVALUATED.

Indications and Usage (Uses)

Updated to

 Reduces the duration and severity of common cold symptoms
 Temporarily relieves symptoms of common cold, including:
 sneezing  runny nose  congestion
 cough  sore throat  headache
 watery eyes  fever  chills

Dosage and Administration

Directions

Adults and children
12 years and over

Dissolve 2 tablets under tongue every 4 hours until relieved.

Children 6 years
to under 12 years

Dissolve 1 tablet under tongue every 4 hours until relieved.

PACKAGE LABEL- PRINCIPAL DISPLAY PANEL

HOMEOPATHIC
NDC 54973-3010-1

AGES 6+

SINCE 1903

Hyland's

Cold Tablets

with Zinc*

SHORTENS

COLDS

MULTI - SYMPTOM RELIEF

Relieves Runny Nose, Congestion, Sore Throat,
Cough, Sneezing, Headache and Fever

Free of Dyes and Preservatives
Non-Drowsy

50 QUICK-DISSOLVING

TABLETS

NATURAL

RELIEF

*SEE NOTE ON SIDE PANEL BELOW DRUGS FACTS